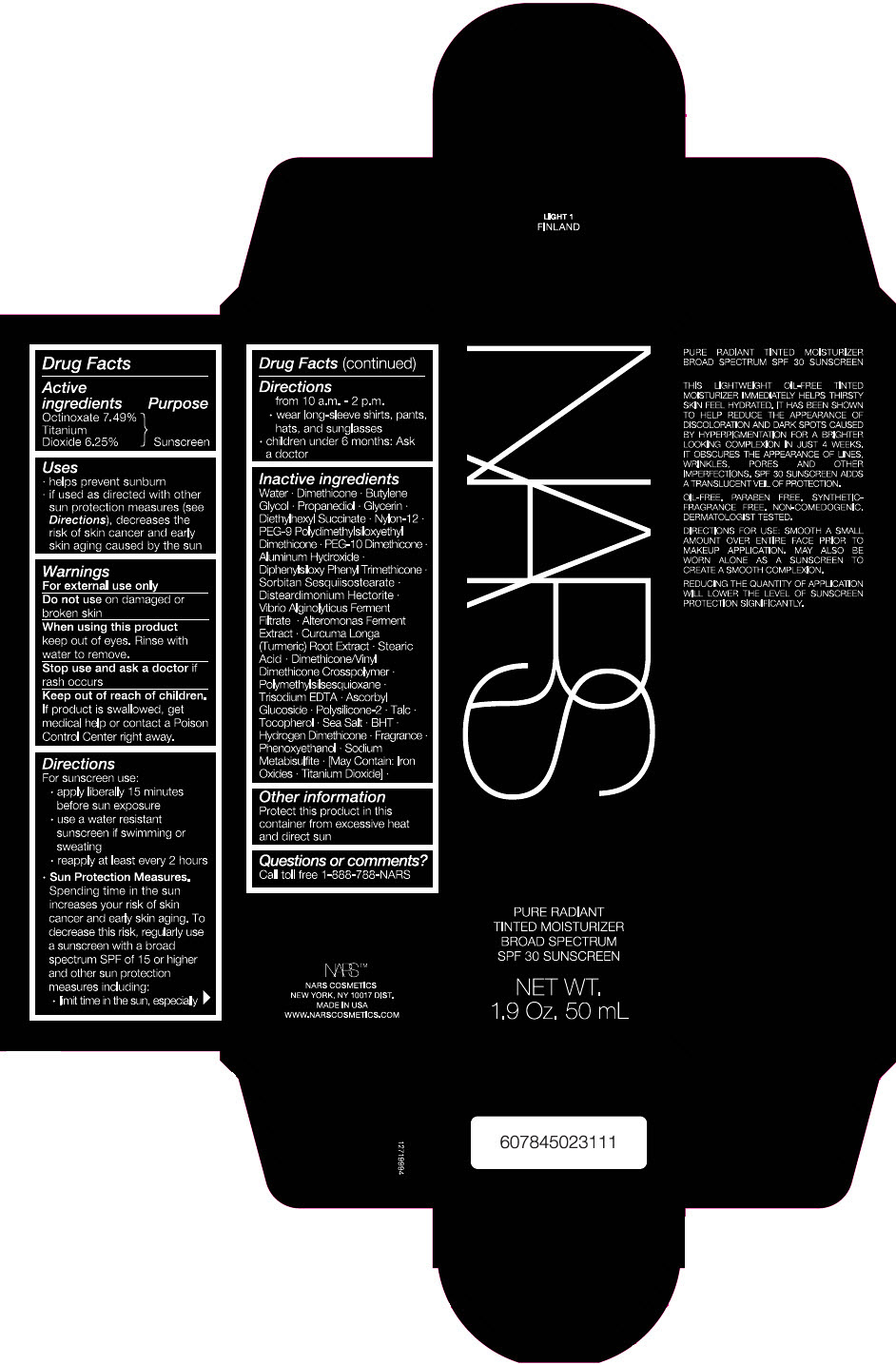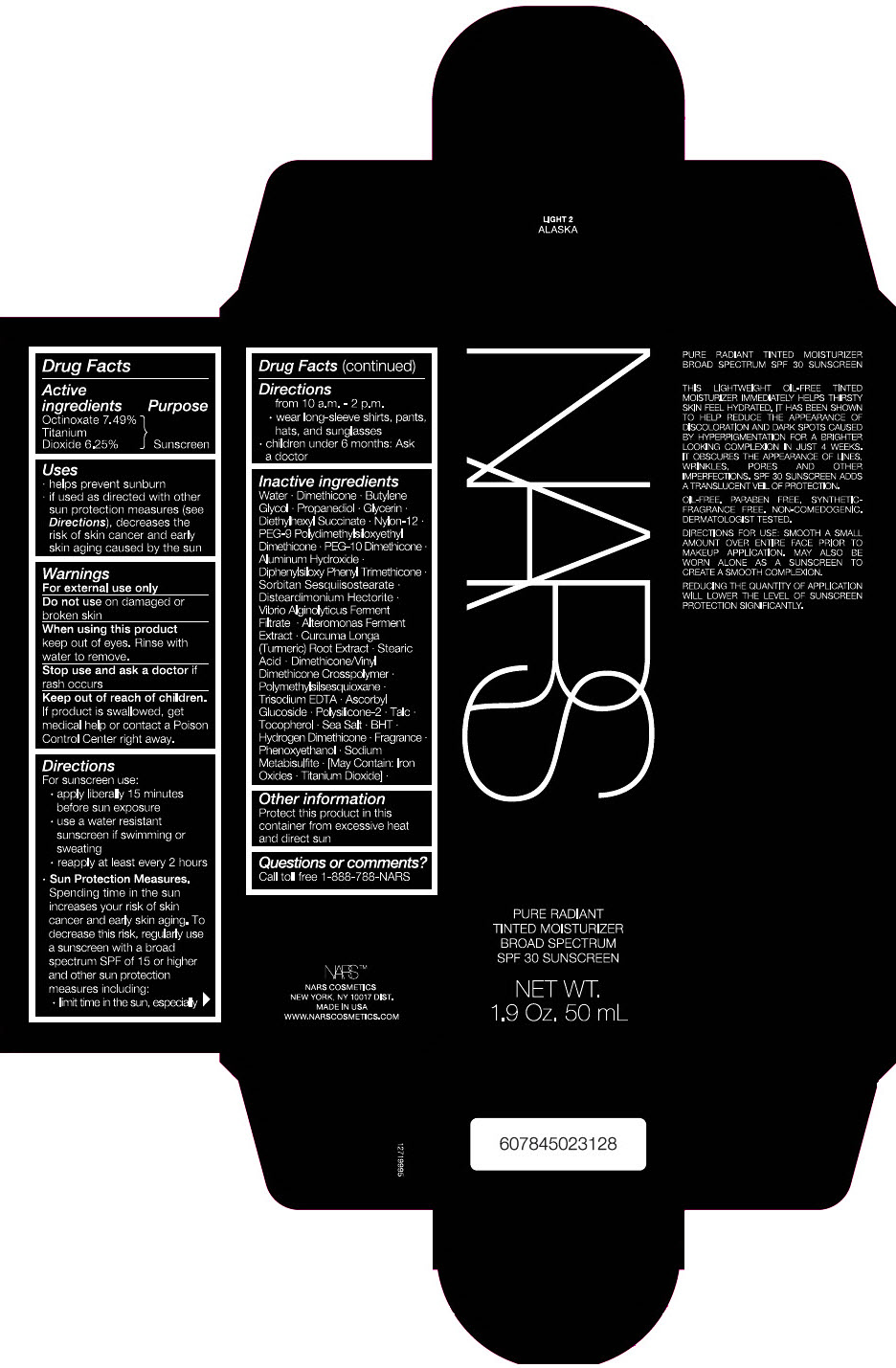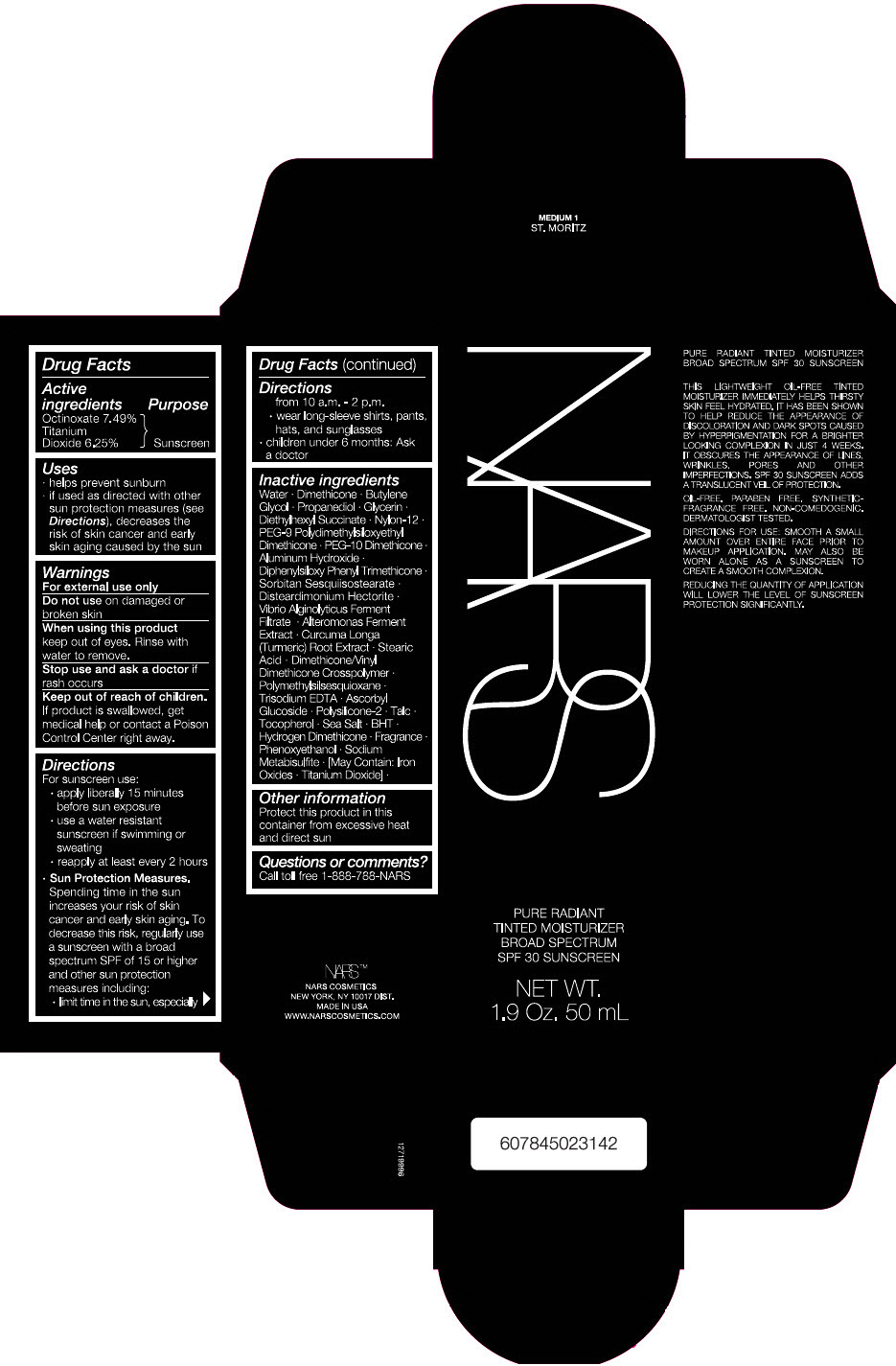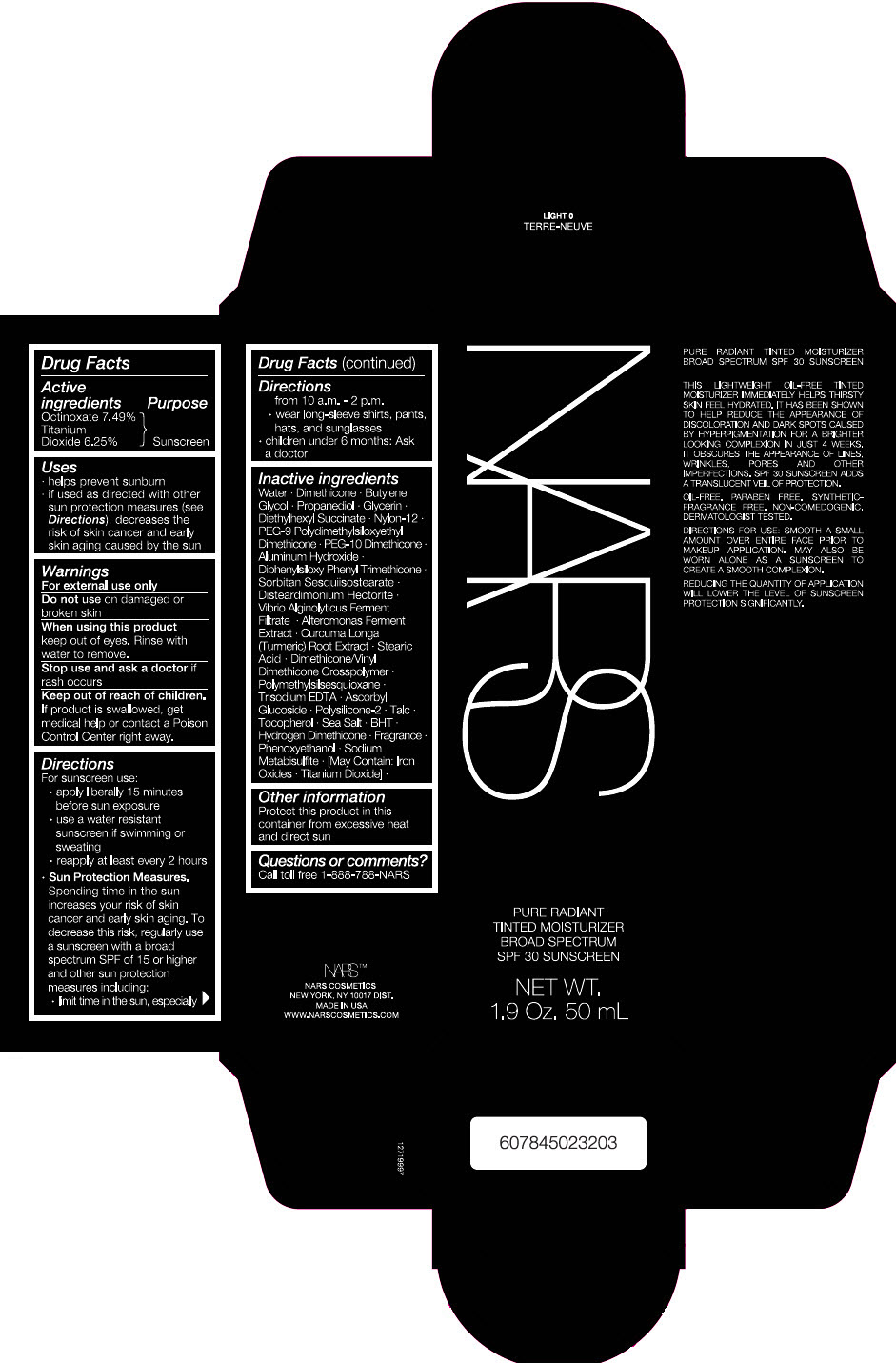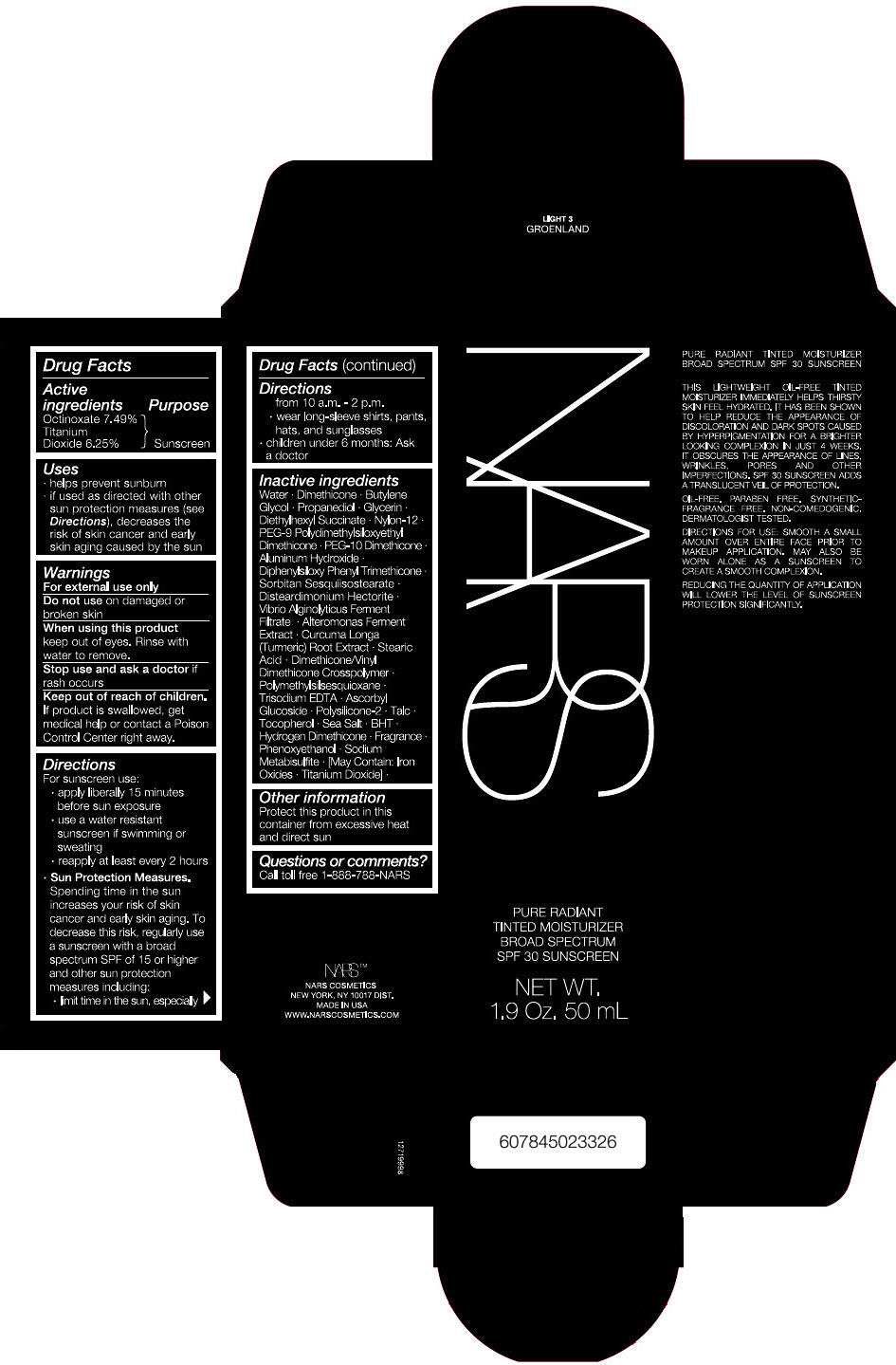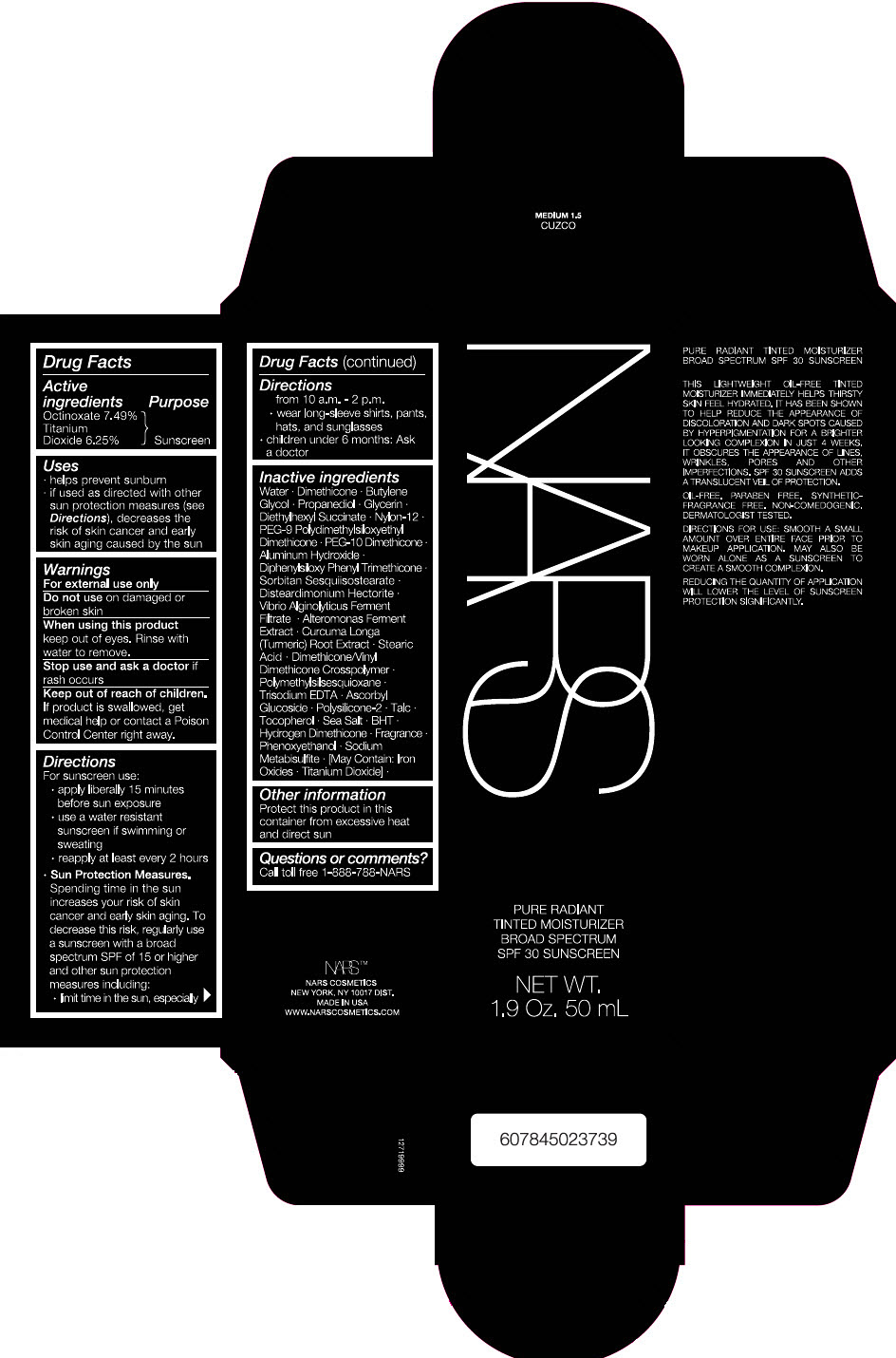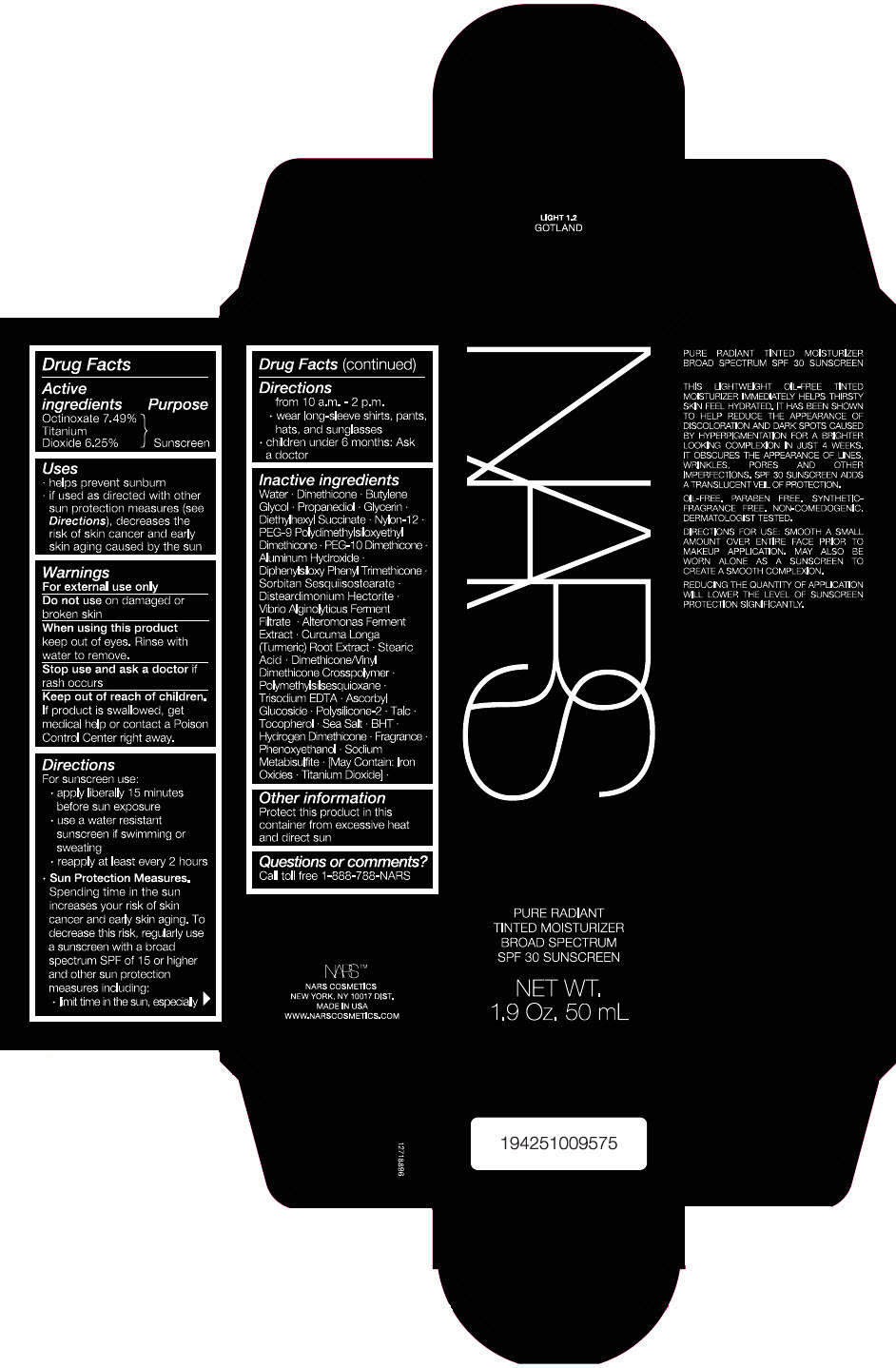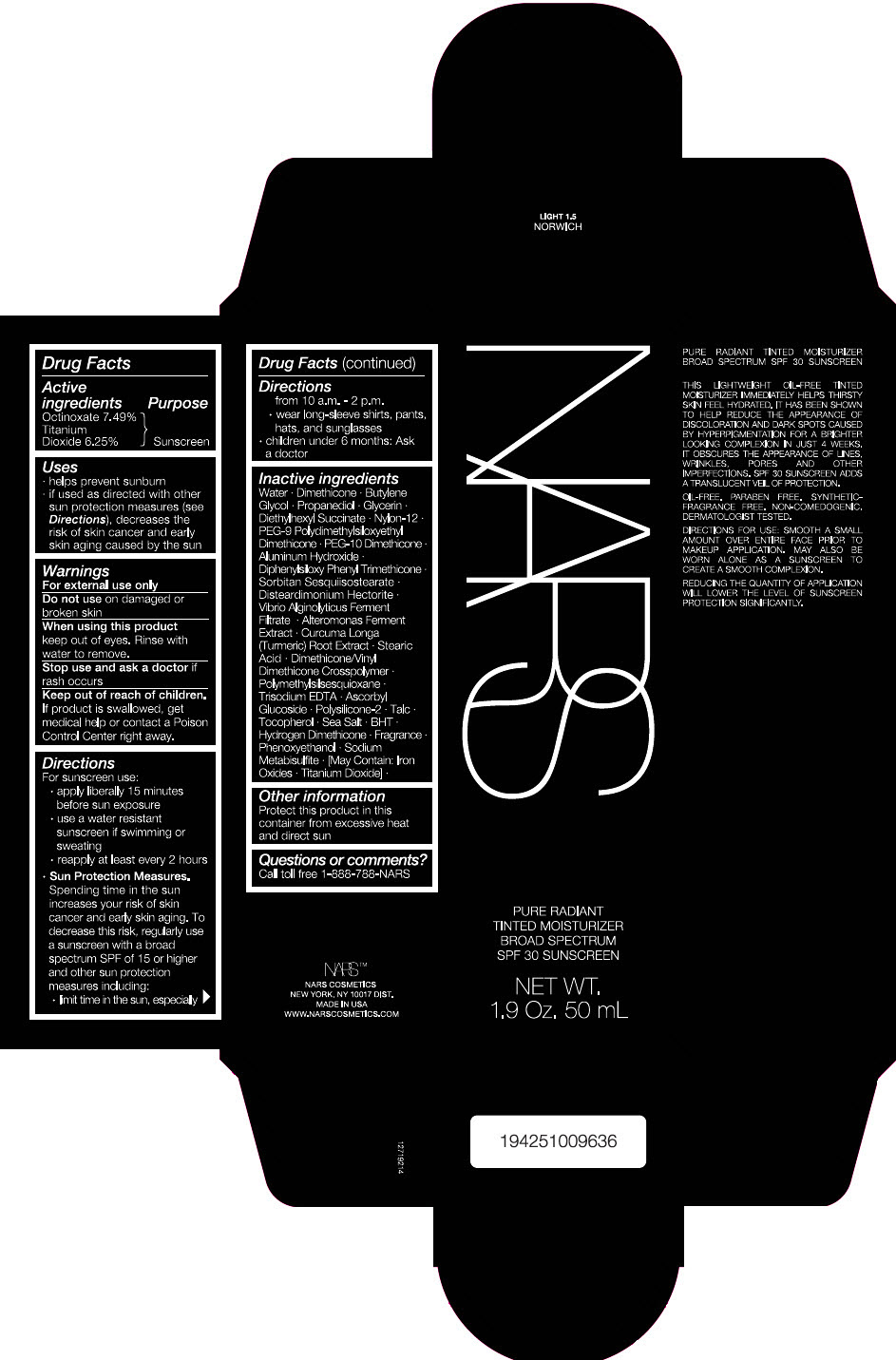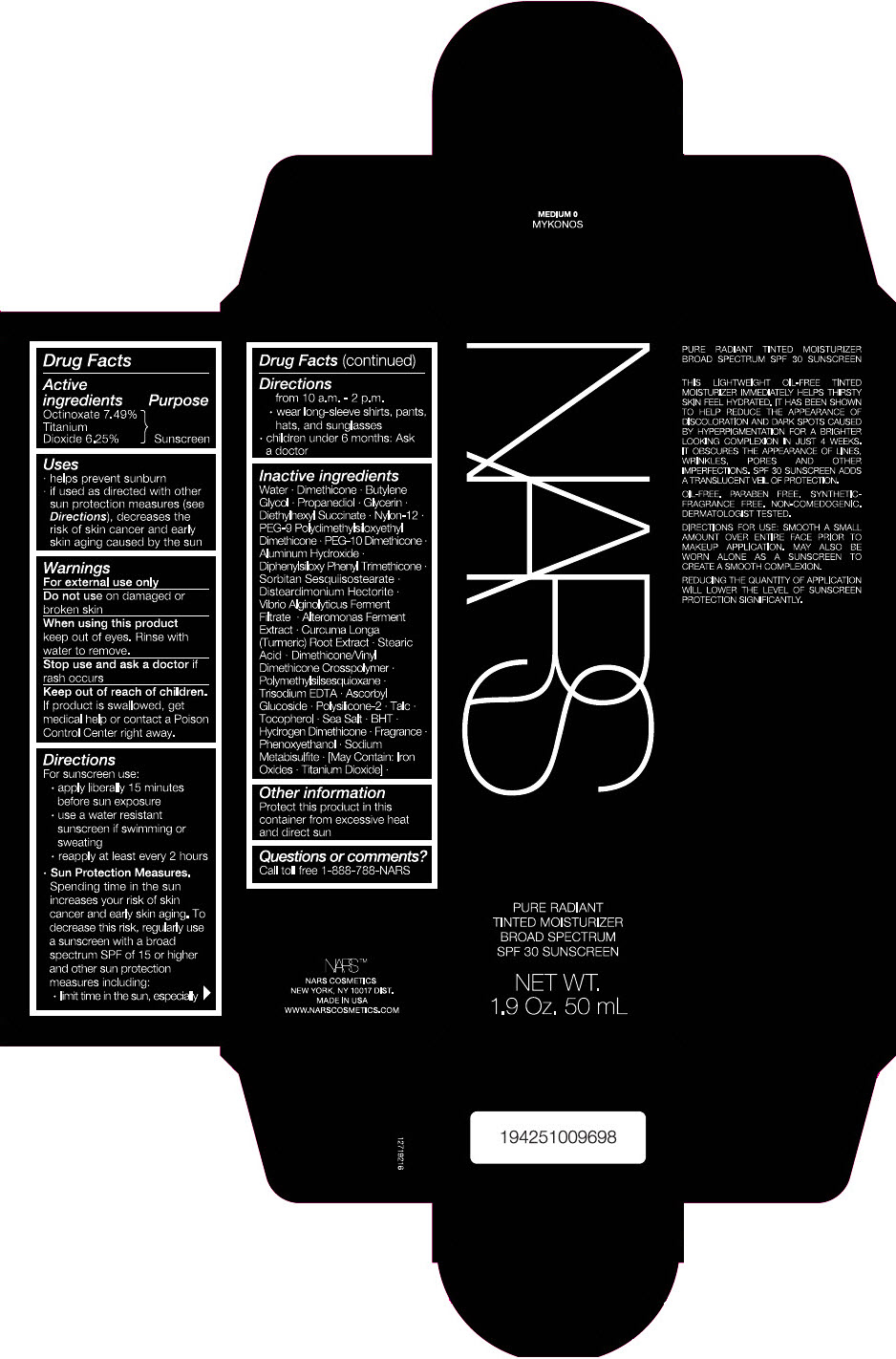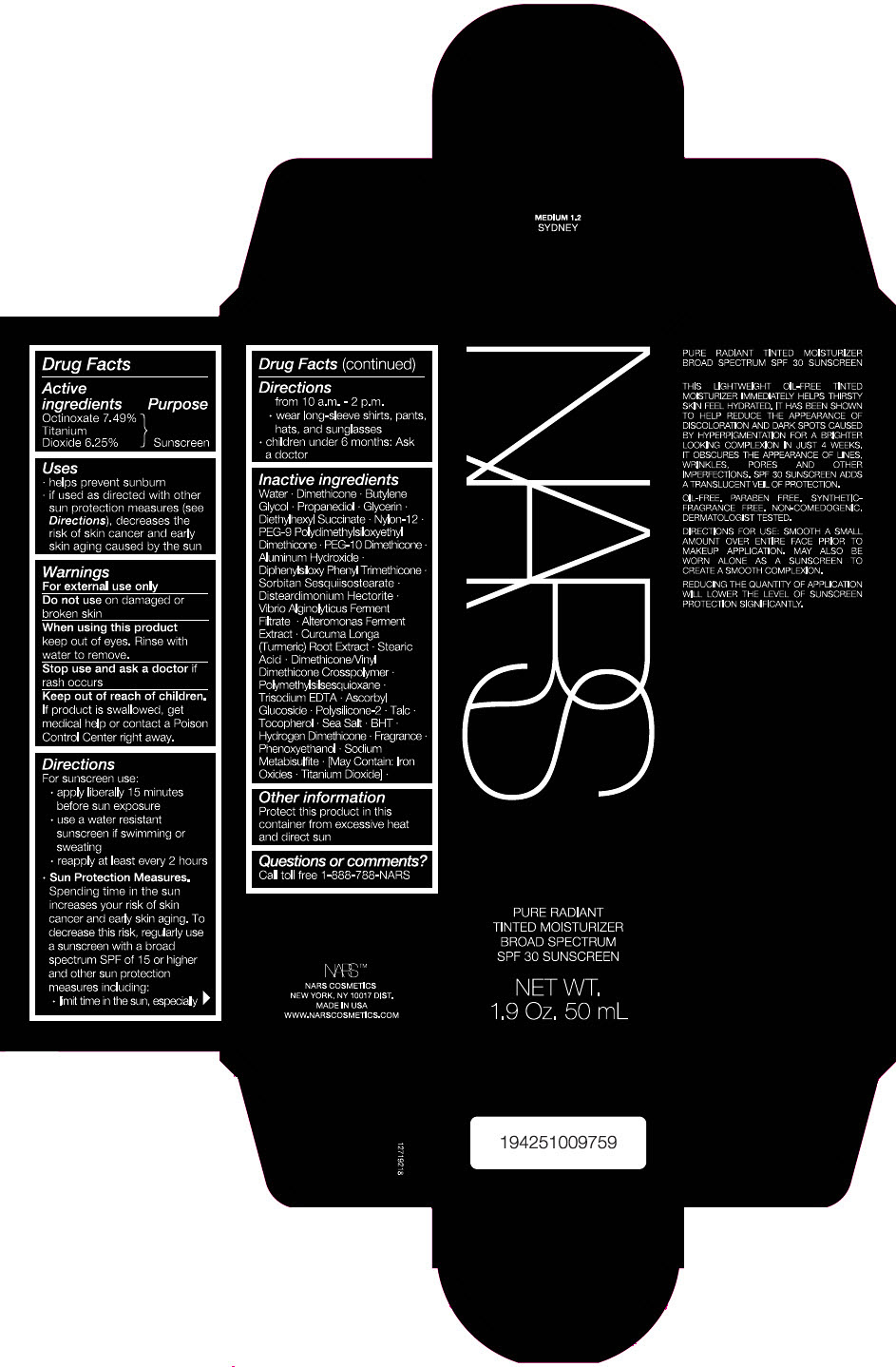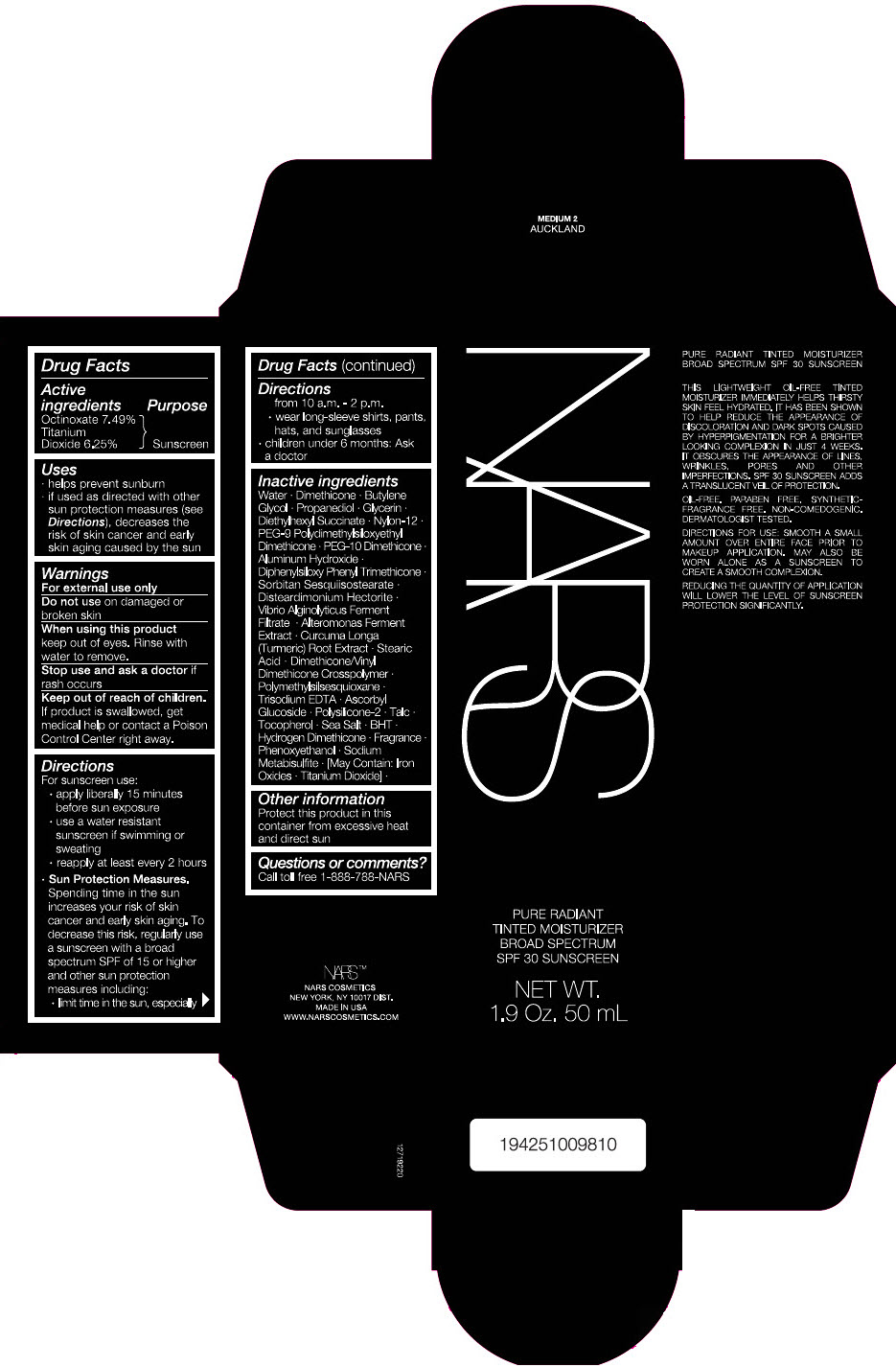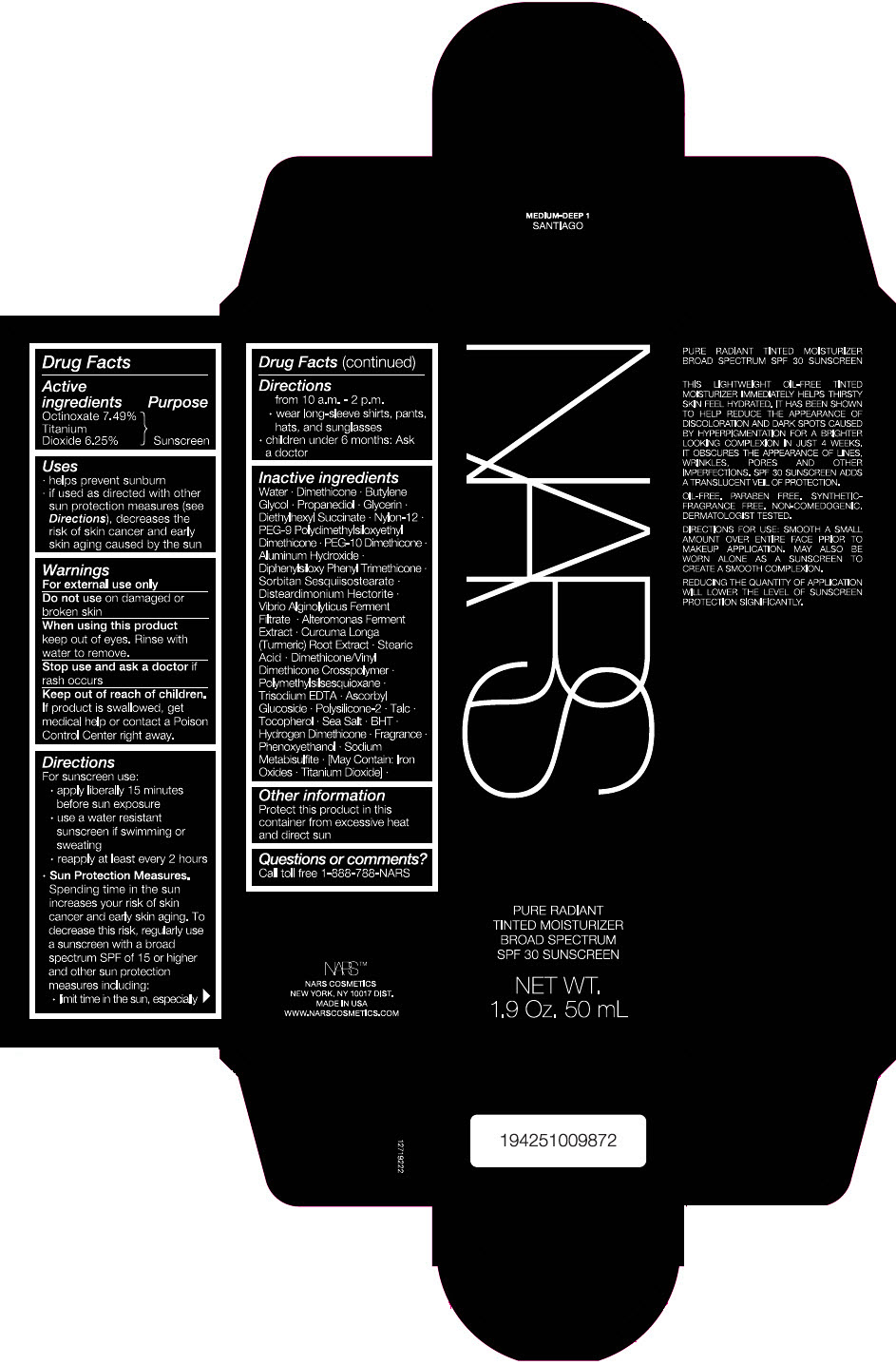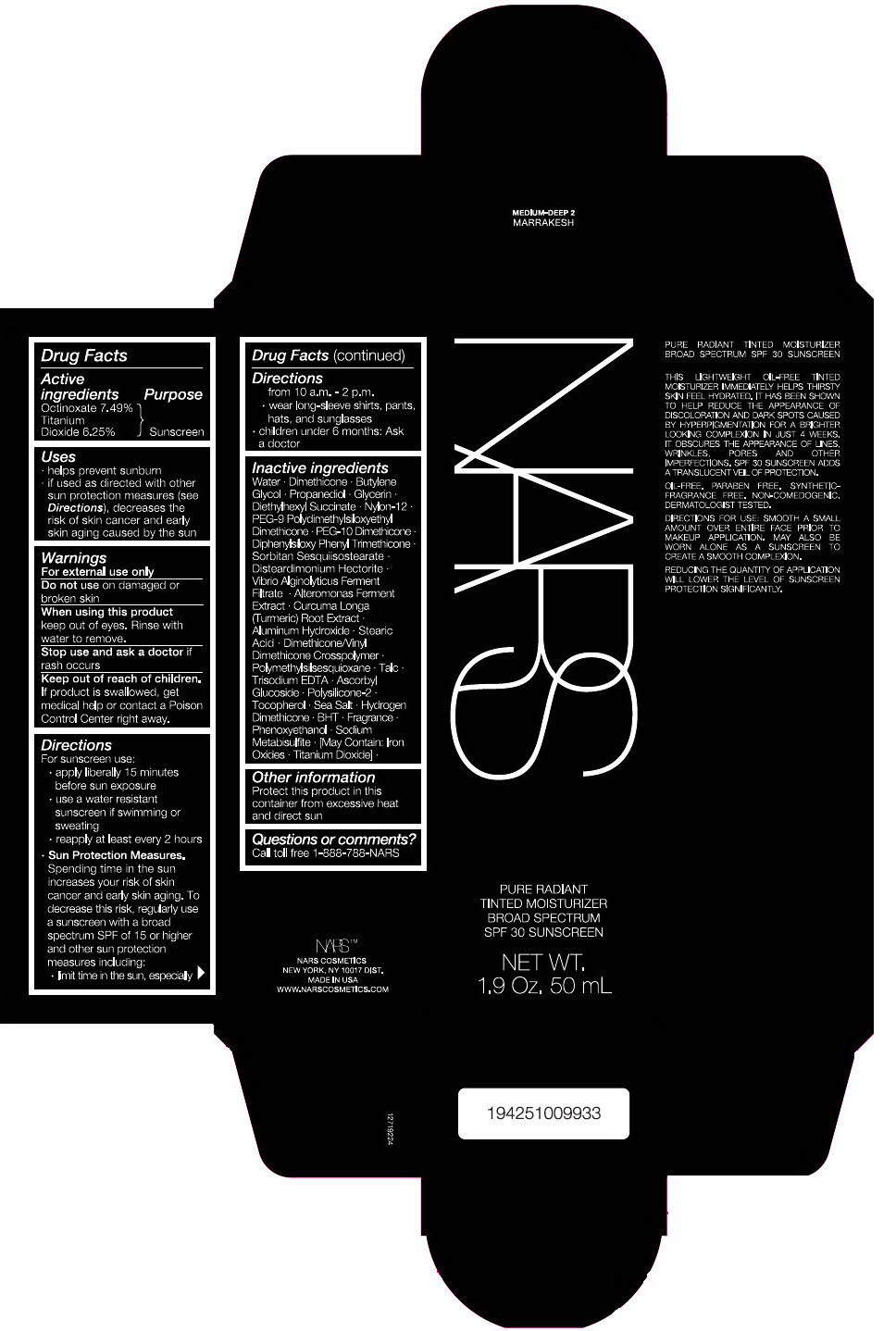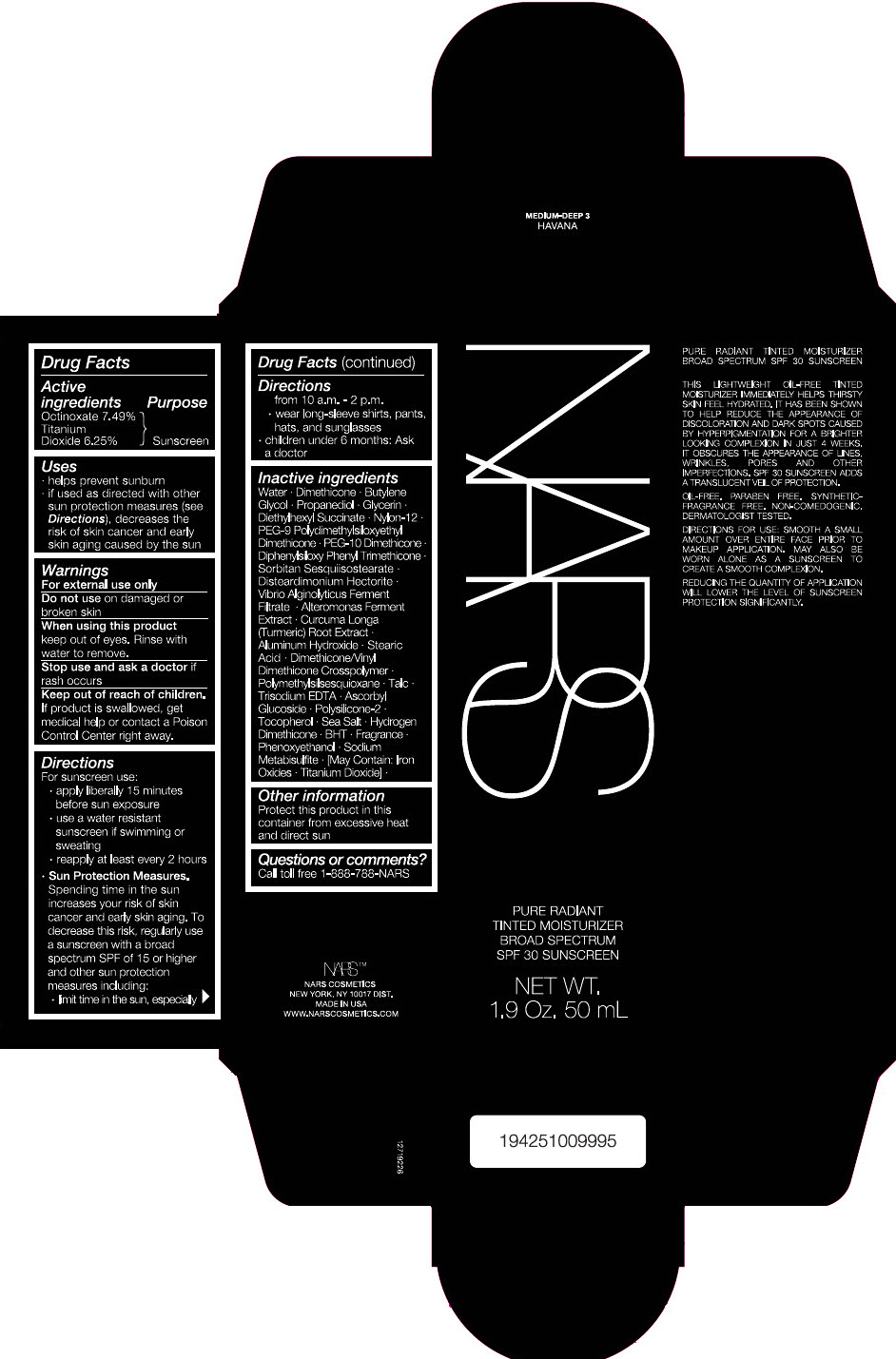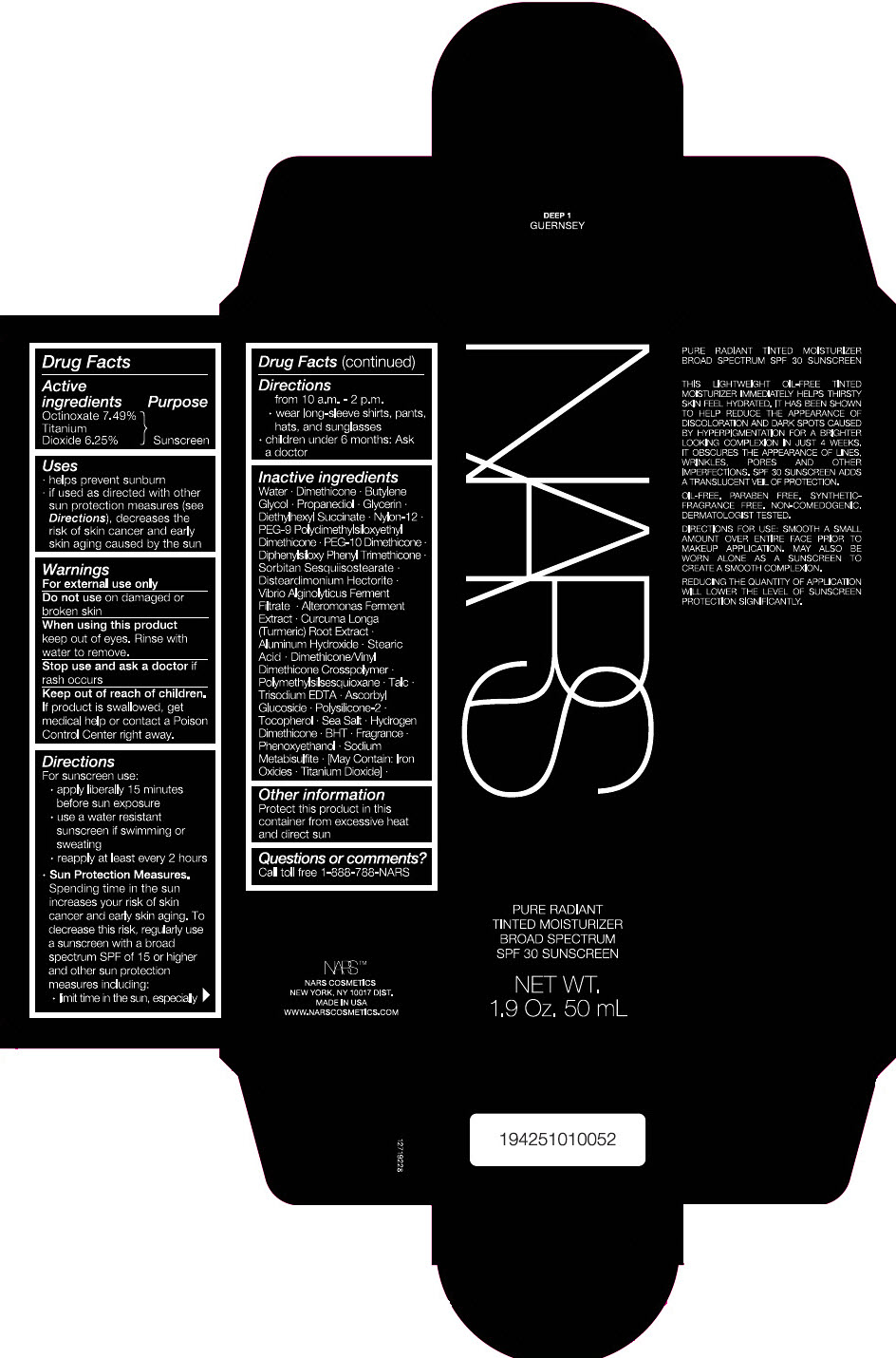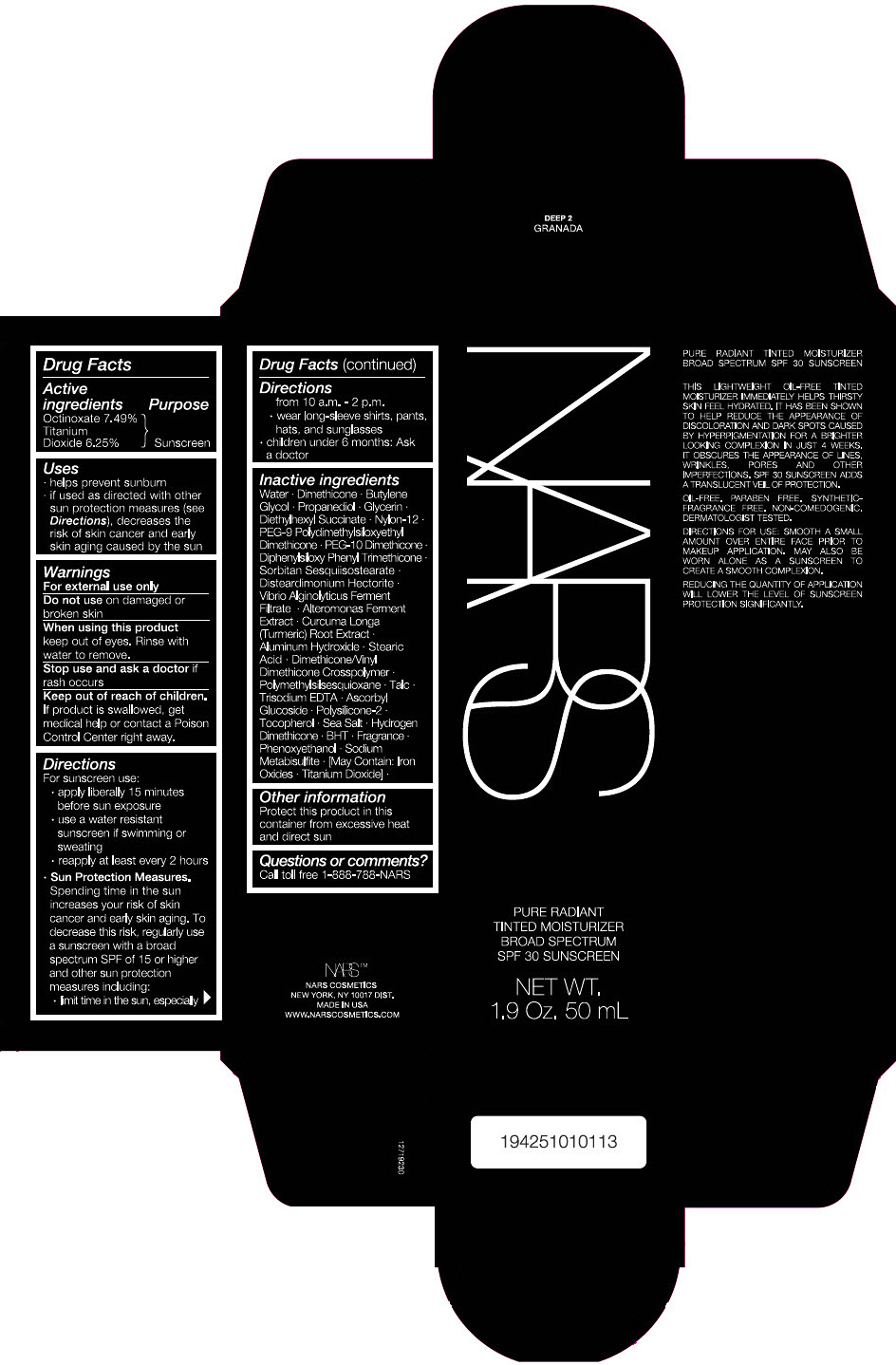 DRUG LABEL: NARS PURE RADIANT TINTED MOISTURIZER FINLAND
NDC: 13734-171 | Form: CREAM
Manufacturer: NARS Cosmetics
Category: otc | Type: HUMAN OTC DRUG LABEL
Date: 20210316

ACTIVE INGREDIENTS: OCTINOXATE 3.745 g/50 mL; TITANIUM DIOXIDE 3.125 g/50 mL
INACTIVE INGREDIENTS: WATER; DIMETHICONE; BUTYLENE GLYCOL; PROPANEDIOL; GLYCERIN; DIETHYLHEXYL SUCCINATE; NYLON-12; FERRIC OXIDE RED; PEG-9 POLYDIMETHYLSILOXYETHYL DIMETHICONE; PEG-10 DIMETHICONE (600 CST); ALUMINUM HYDROXIDE; DIPHENYLSILOXY PHENYL TRIMETHICONE; SORBITAN SESQUIISOSTEARATE; DISTEARDIMONIUM HECTORITE; STEARIC ACID; DIMETHICONE/VINYL DIMETHICONE CROSSPOLYMER (SOFT PARTICLE); PHENOXYETHANOL; FERRIC OXIDE YELLOW; POLYMETHYLSILSESQUIOXANE (4.5 MICRONS); FERROSOFERRIC OXIDE; EDETATE TRISODIUM; TALC; ASCORBYL GLUCOSIDE; .ALPHA.-TOCOPHEROL; ALTEROMONAS MACLEODII POLYSACCHARIDES; SEA SALT; HYDROGEN DIMETHICONE (13 CST); BUTYLATED HYDROXYTOLUENE; SODIUM METABISULFITE; TURMERIC

NARS PURE RADIANT TINTED MOISTURIZER

Drug Facts

ACTIVE INGREDIENT

Active ingredients | Purpose
Octinoxate 7.49% | Sunscreen
Titanium Dioxide 6.25% | Sunscreen

Uses

- helps prevent sunburn
- if used as directed with other sun protection measures (see Directions), decreases the risk of skin cancer and early skin aging caused by the sun

Warnings

For external use only

Do not use on damaged or broken skin

When using this product keep out of eyes. Rinse with water to remove.

Stop use and ask a doctor if rash occurs

Keep out of reach of children. If product is swallowed, get medical help or contact a Poison Control Center right away.

Directions

For sunscreen use:

- apply liberally 15 minutes before sun exposure
- use a water resistant sunscreen if swimming or sweating
- reapply at least every 2 hours
- Sun Protection Measures. Spending time in the sun increases your risk of skin cancer and early skin aging. To decrease this risk, regularly use a sunscreen with a broad spectrum SPF of 15 or higher and other sun protection measures including:
  - limit time in the sun, especially from 10 a.m. – 2 p.m.
  - wear long-sleeve shirts, pants, hats, and sunglasses
- children under 6 months: Ask a doctor

Inactive Ingredients

Water ∙ Dimethicone ∙ Butylene Glycol ∙ Propanediol ∙ Glycerin ∙ Diethylhexyl Succinate ∙ Nylon-12 ∙ PEG-9 Polydimethylsiloxyethyl Dimethicone ∙ PEG-10 Dimethicone ∙ Aluminum Hydroxide ∙ Diphenylsiloxy Phenyl Trimethicone ∙ Sorbitan Sesquiisostearate ∙ Disteardimonium Hectorite ∙ Vibrio Alginolyticus Ferment Filtrate ∙ Alteromonas Ferment Filtrate ∙ Curcuma Longa (Turmeric) Root Extract ∙ Stearic Acid ∙ Dimethicone/Vinyl Dimethicone Crosspolymer ∙ Polymethylsilsesquioxane ∙ Trisodium EDTA ∙ Ascorbyl Glucoside ∙ Polysilicone-2 ∙ Talc ∙ Tocopherol ∙ Sea Salt ∙ BHT ∙ Hydrogen Dimethicone ∙ Fragrance ∙ Phenoxyethanol ∙ Sodium Metabisulfite ∙ Potassium Sorbate ∙ [(May Contain): Titanium Dioxide ∙ Iron Oxides] ∙

Other information

Protect this product in this container from excessive heat and direct sun

Questions or comments?

Call toll free 1-888-788-NARS

PRINCIPAL DISPLAY PANEL - 50 mL Tube Carton - LIGHT 1 - FINLAND

NARS

PURE RADIANT
TINTED MOISTURIZER
BROAD SPECTRUM
SPF 30 SUNSCREEN

NET WT.
1.9 Oz. 50 mL

PRINCIPAL DISPLAY PANEL - 50 mL Tube Carton - LIGHT 2 - ALASKA

NARS

PURE RADIANT
TINTED MOISTURIZER
BROAD SPECTRUM
SPF 30 SUNSCREEN

NET WT.
1.9 Oz. 50 mL

PRINCIPAL DISPLAY PANEL - 50 mL Tube Carton - MEDIUM 1 - ST. MORITZ

NARS

PURE RADIANT
TINTED MOISTURIZER
BROAD SPECTRUM
SPF 30 SUNSCREEN

NET WT.
1.9 Oz. 50 mL

PRINCIPAL DISPLAY PANEL - 50 mL Tube Carton - LIGHT 0 - TERRE-NEUVE

NARS

PURE RADIANT
TINTED MOISTURIZER
BROAD SPECTRUM
SPF 30 SUNSCREEN

NET WT.
1.9 Oz. 50 mL

PRINCIPAL DISPLAY PANEL - 50 mL Tube Carton - LIGHT 3 - GROENLAND

NARS

PURE RADIANT
TINTED MOISTURIZER
BROAD SPECTRUM
SPF 30 SUNSCREEN

NET WT.
1.9 Oz. 50 mL

PRINCIPAL DISPLAY PANEL - 50 mL Tube Carton - MEDIUM 1.5 - CUZCO

NARS

PURE RADIANT
TINTED MOISTURIZER
BROAD SPECTRUM
SPF 30 SUNSCREEN

NET WT.
1.9 Oz. 50 mL

PRINCIPAL DISPLAY PANEL - 50 mL Tube Carton - LIGHT 1.2 - GOTLAND

NARS

PURE RADIANT
TINTED MOISTURIZER
BROAD SPECTRUM
SPF 30 SUNSCREEN

NET WT.
1.9 Oz. 50 mL

PRINCIPAL DISPLAY PANEL - 50 mL Tube Carton - LIGHT 1.5 - NORWICH

NARS

PURE RADIANT
TINTED MOISTURIZER
BROAD SPECTRUM
SPF 30 SUNSCREEN

NET WT.
1.9 Oz. 50 mL

PRINCIPAL DISPLAY PANEL - 50 mL Tube Carton - MEDIUM 0 - MYKONOS

NARS

PURE RADIANT
TINTED MOISTURIZER
BROAD SPECTRUM
SPF 30 SUNSCREEN

NET WT.
1.9 Oz. 50 mL

PRINCIPAL DISPLAY PANEL - 50 mL Tube Carton - MEDIUM 1.2 - SYDNEY

NARS

PURE RADIANT
TINTED MOISTURIZER
BROAD SPECTRUM
SPF 30 SUNSCREEN

NET WT.
1.9 Oz. 50 mL

PRINCIPAL DISPLAY PANEL - 50 mL Tube Carton - MEDIUM 2 - AUCKLAND

NARS

PURE RADIANT
TINTED MOISTURIZER
BROAD SPECTRUM
SPF 30 SUNSCREEN

NET WT.
1.9 Oz. 50 mL

PRINCIPAL DISPLAY PANEL - 50 mL Tube Carton - MEDIUM-DEEP 1 - SANTIAGO

NARS

PURE RADIANT
TINTED MOISTURIZER
BROAD SPECTRUM
SPF 30 SUNSCREEN

NET WT.
1.9 Oz. 50 mL

PRINCIPAL DISPLAY PANEL - 50 mL Tube Carton - MEDIUM-DEEP 2 - MARRAKESH

NARS

PURE RADIANT
TINTED MOISTURIZER
BROAD SPECTRUM
SPF 30 SUNSCREEN

NET WT.
1.9 Oz. 50 mL

PRINCIPAL DISPLAY PANEL - 50 mL Tube Carton - MEDIUM-DEEP 3 - HAVANA

NARS

PURE RADIANT
TINTED MOISTURIZER
BROAD SPECTRUM
SPF 30 SUNSCREEN

NET WT.
1.9 Oz. 50 mL

PRINCIPAL DISPLAY PANEL - 50 mL Tube Carton - DEEP 1 - GUERNSEY

NARS

PURE RADIANT
TINTED MOISTURIZER
BROAD SPECTRUM
SPF 30 SUNSCREEN

NET WT.
1.9 Oz. 50 mL

PRINCIPAL DISPLAY PANEL - 50 mL Tube Carton - DEEP 2 - GRANADA

NARS

PURE RADIANT
TINTED MOISTURIZER
BROAD SPECTRUM
SPF 30 SUNSCREEN

NET WT.
1.9 Oz. 50 mL